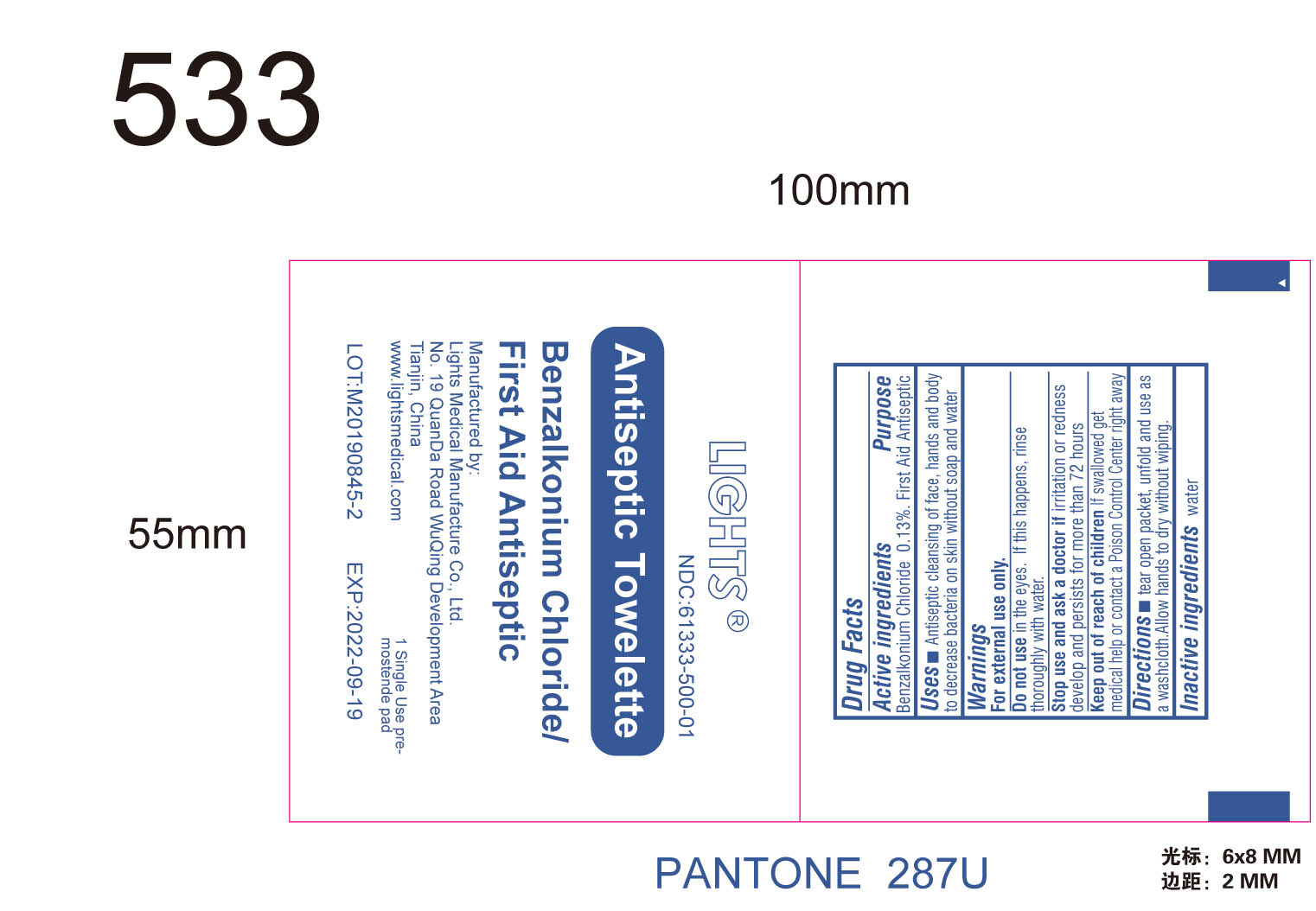 DRUG LABEL: BZK Antiseptic
NDC: 61333-500 | Form: SWAB
Manufacturer: Lights Medical Manufacture Co., Ltd.
Category: otc | Type: HUMAN OTC DRUG LABEL
Date: 20260121

ACTIVE INGREDIENTS: BENZALKONIUM CHLORIDE 0.13 mg/100 mg
INACTIVE INGREDIENTS: WATER

61333-500 BZK Antiseptic Swab

Active ingredient

benzalkonium chloride 0.13%

Purpose

First aid antiseptic

Uses

Antiseptic cleaning of face, hands and body without soap and water.

Warnings

For external use only.

Do not use in the eyes. If this happens, rinse thoroughly with water

Stop use and ask a doctor if irritation or redness develops and persists for more than 72 hours

Keep out of reach of children
If swallowed, get medical help or contact a Poison Control Center right away.

Directions

Tear open packet, unfold and use as a washcloth. Allow hands to dry with wiping

INACTIVE INGREDIENT

Water